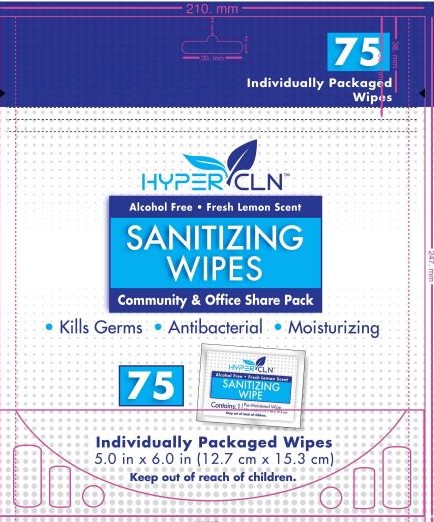 DRUG LABEL: Hypercln Sanitary Wipes
NDC: 78847-321 | Form: CLOTH
Manufacturer: Falcon Safety Products, Inc.
Category: otc | Type: HUMAN OTC DRUG LABEL
Date: 20200714

ACTIVE INGREDIENTS: BENZALKONIUM CHLORIDE 0.0013 1/1 1
INACTIVE INGREDIENTS: EUCALYPTOL; ALOE VERA LEAF; ANHYDROUS CITRIC ACID; PANTHENOL; CITRONITRILE; ALLANTOIN; PEG-12 DIMETHICONE; WATER; DECYL GLUCOSIDE; .ALPHA.-TOCOPHEROL ACETATE; 3,7-DIMETHYL-1-OCTANOL; GLYCERIN; POTASSIUM SORBATE; 3,3'-DIHYDROXYDIPROPYL ETHER; TETRAHYDROLINALOOL; EDETATE SODIUM; SODIUM BENZOATE; SODIUM HYDROXYMETHYLGLYCINATE; CHAMOMILE

Hypercln Sanitizing Wipes

Active Ingredient

Benzalkonium chloride 0.13%

Purpose

Anti-bacterial

Warning

Warnings

For external use only.

When using this product avoid contact with eyes. If in eyes, flush thoroughly with water.

Stop and ask a doctor if:

• irritation develops. • condition persists for more than 72 hours.

Keep out of the reach of children.

Keep out of reach of children. If swallowed, get medical help or contact a Poison Control right away.

Inactive ingredients

Inactive Ingredients: Water, Decyl Glucoside, Glycerin, Sodium hydroxymethylglycinate, Citric Acid, PEG-12 Dimethicone, Fragrance, Sodium Benzoate, Potassium Sorbate, Allantoin, Tocopheryl Acetate, Aloe Barbadensis Leaf Water, Chamomilla Recutita (Matricaria) Flower Water, Panthenol, Tetrasodium EDTA, Benzyl Alcohol, Sodium Hydroxide

Indications

Hand sanitizer to help reduce bacteria on skin.

Directions

To Use: open, unfold and apply. Sanitize hands or other affected area. Discard in trash after use. Do not flush.